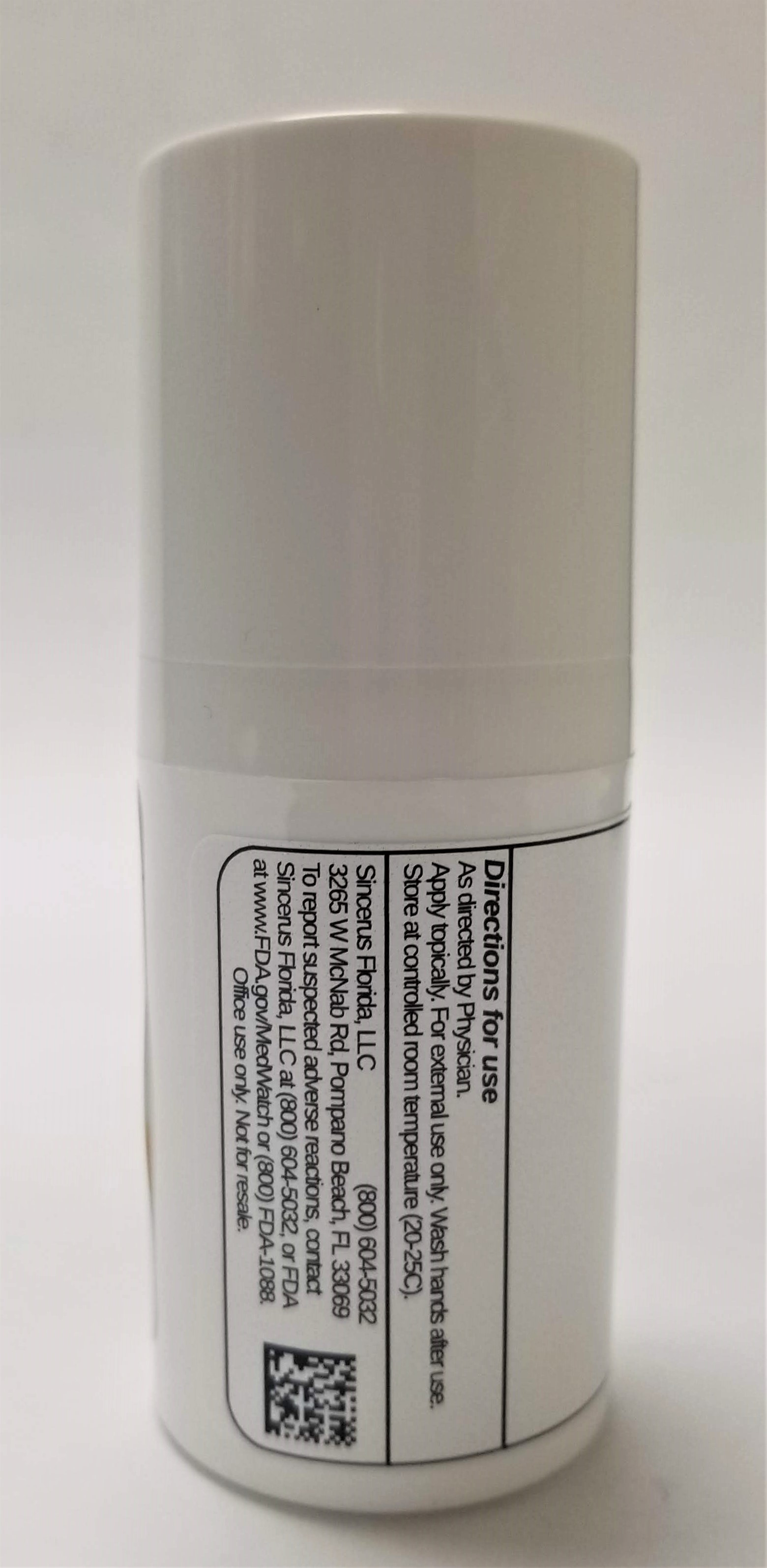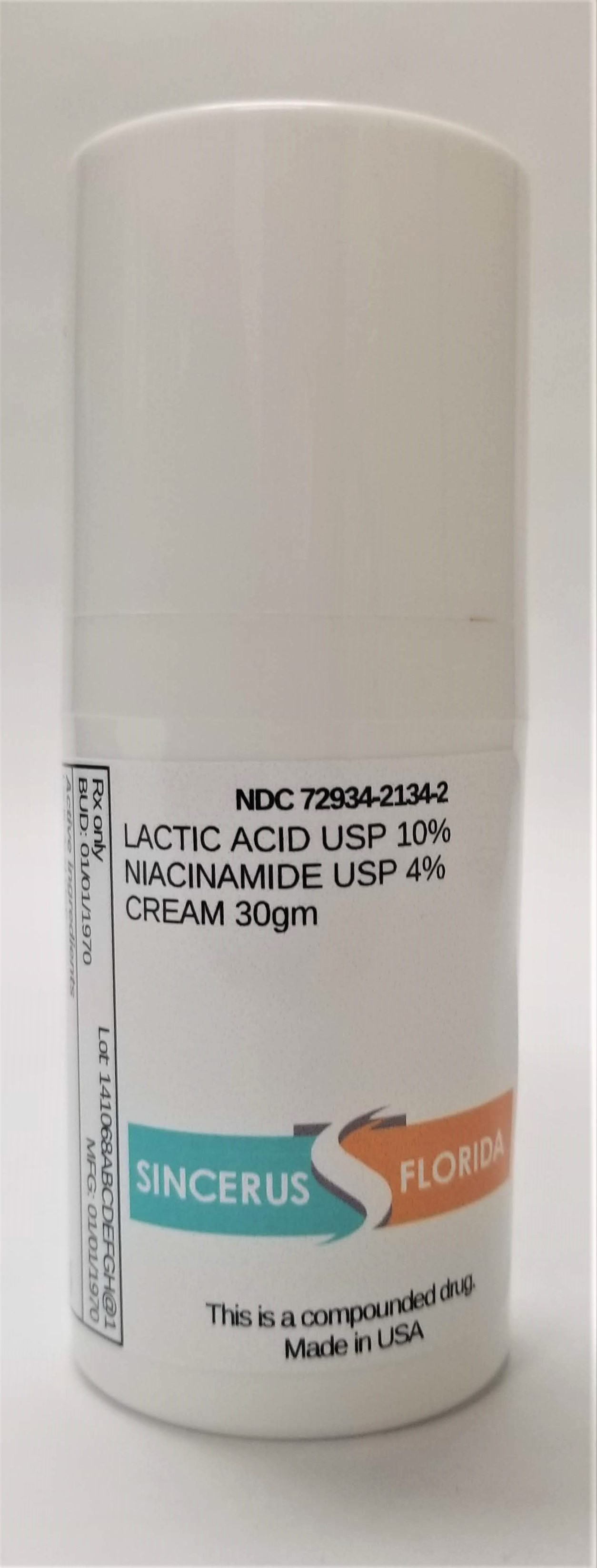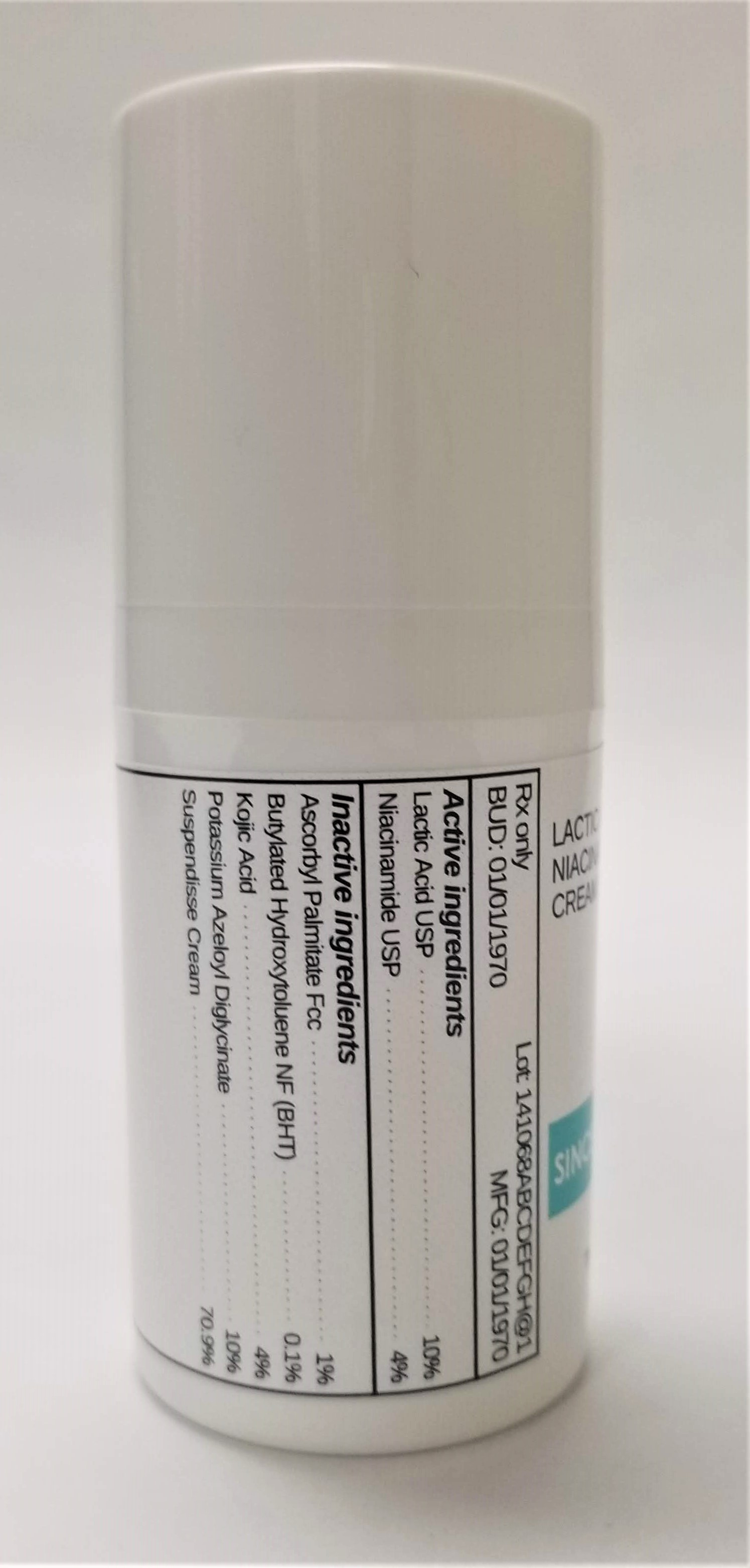 DRUG LABEL: LACTIC ACID 10% / NIACINAMIDE 4%
NDC: 72934-2134 | Form: CREAM
Manufacturer: Sincerus Florida, LLC
Category: prescription | Type: HUMAN PRESCRIPTION DRUG LABEL
Date: 20190424

ACTIVE INGREDIENTS: NIACINAMIDE 4 g/100 g; LACTIC ACID 10 g/100 g

LACTIC ACID 10% / NIACINAMIDE 4%